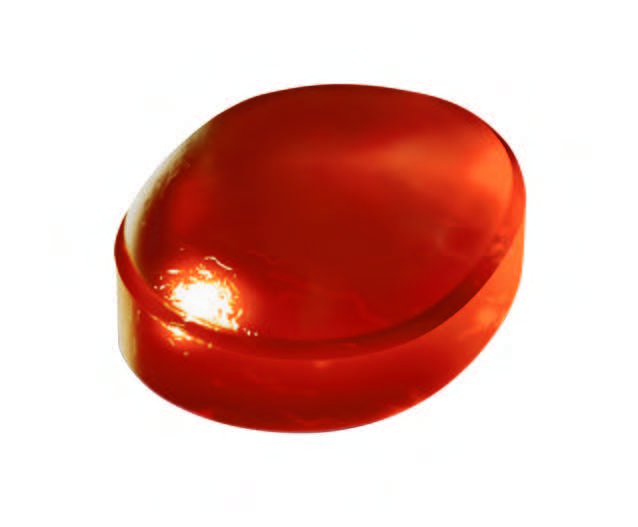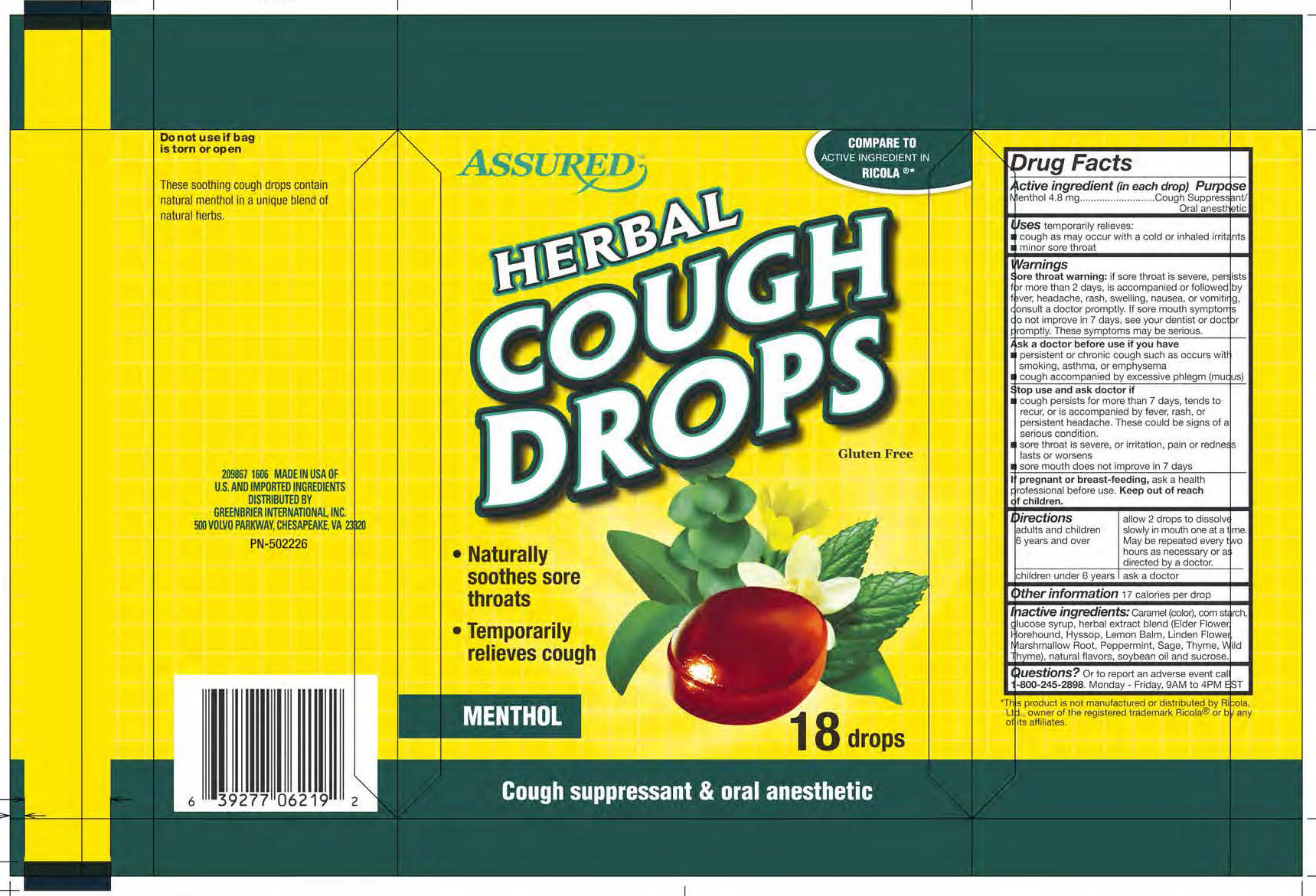 DRUG LABEL: Herbal cough drops
NDC: 33992-1014 | Form: LOZENGE
Manufacturer: Greenbrier International Inc.
Category: otc | Type: HUMAN OTC DRUG LABEL
Date: 20211101

ACTIVE INGREDIENTS: MENTHOL 4.8 mg/1 1
INACTIVE INGREDIENTS: WATER

Menthol 4.8 mg

Active ingredient (in each drop)

Menthol 4.8 mg

Purpose

Cough suppressant / Oral anesthetic

INDICATIONS AND USAGE

Uses temporarily relieves:

cough as may ocur with a cold or inhaled irritants

minor sore throat

Warnings

Sore throat warning: if sore throat is severe, persists for more than 2 days, is accompanied or followed by fever, headache, rash, swelling, nausea, or vomiting, consult a doctor promptly. If sore mouth symptoms do not improve in 7 days, see your dentist or doctor promptly. These symptoms may be serious.

Ask a doctor before use if you have:

- persistent or chronic cough such as occurs with smoking, asthma, or emphysema

- cough accompanied by excessive phlegm (mucus)

Stop use and ask doctor if

- cough persists for more than 7 days, tends to recur, or is accompanied by fever, rash, or persistent headache. These could be signs of a serious condition.

- sore throat is severe, or irritation, pain or redness lasts or worsens

- sore mouth does not improve in 7 days

PREGNANCY OR BREAST FEEDING

If pregnant or breast-feeding, ask a health professional before use.

Keep out of reach of children.

Directions

adults and children 6 years and over - allow 2 drops to dissolve slowly in mouth, one at a time. May be repeated every 2 hours as necessary or as directed by a doctor.

children under 6 years - ask a doctor

Other information

17 calories per drop

INACTIVE INGREDIENT

Inactive ingredients: Caramel, corn starch, glucose syrup, herbal extract blend (Elderflower, Horehould, Hyssop, Lemon Balm, Linden Flower, Marshmallow Root, Peppermint, Sage, Thyme, Wild Thyme), natural flavors, soybean oil, and sucrose.

QUESTIONS

Questions? Or to report an adverse event call 1-800-245-2898. Monday - Friday, 9AM to 4PM EST